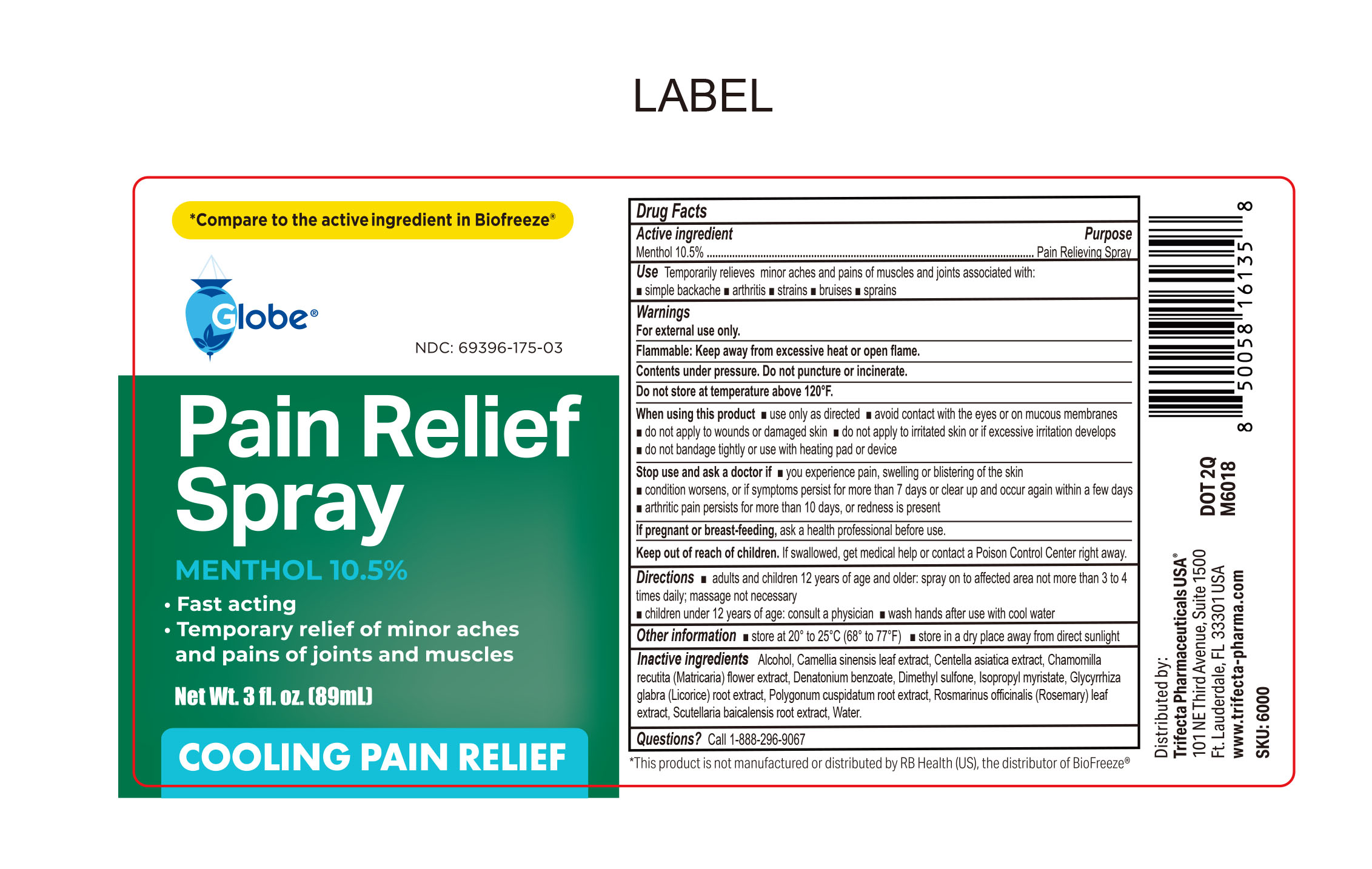 DRUG LABEL: Pain Relief
NDC: 69396-175 | Form: SPRAY
Manufacturer: Trifecta Pharmaceuticals USA, LLC.
Category: otc | Type: HUMAN OTC DRUG LABEL
Date: 20260217

ACTIVE INGREDIENTS: MENTHOL 10.5 g/100 mL
INACTIVE INGREDIENTS: ALCOHOL; CAMELLIA SINENSIS LEAF; MATRICARIA RECUTITA FLOWERING TOP; POLYGONUM CUSPIDATUM ROOT; WATER; GLYCYRRHIZA GLABRA (LICORICE) ROOT POWDER; ROSEMARY; CENTELLA ASIATICA TRITERPENOIDS; DIMETHYL SULFONE; ISOPROPYL MYRISTATE; SCUTELLARIA BAICALENSIS ROOT; DENATONIUM BENZOATE

Globe Pain Relief Spray

Active Ingredient

Menthol 10.5%

Purpose

Pain Relieving Spray

Indication

Temporary Relief of minor aches and pains of joints and muscles associated with

- simple backache
- arthritis
- strains
- bruises
- sprains

Warnings

For External Use Only

Contents under pressure. Do not puncture or incinerate

Flammable: Keep away from excessive heat or open flame.

Do not store at temperature above 120ºF.

Stop use and ask a doctor

- If you experience pain, swelling or blistering of the skin.
- Condition worsens or if symptoms persist for more than 7 days or clear up and occur again within a few days
- Arthritic pain persists for more than 10 days or redness is present

Keep out of the reach of children

If swallowed, get medical help or contact a Poison Control Center right away.

Directions

Adults and Children:

12 years of age and older, spray on to affected area not more than 3 to 4 times daily. Massage not necessary.

Children under 12 years of age: consult a physician

wash hands after use with cool water

When using this product

- use only as directed
- avoid contact with the eyes or on mucous membranes
- do not apply to wounds or damaged skin
- do not apply to irritated skin or if ecessive irritation develops
- do not bandage tightly or use with heating pad or device

Other information

- Store at (20º-25ºC) (68ºF - 77ºF).
- Store in a dry place away from direct sunlight

If Pregnant or breast feeding

Ask a health professional before use.

Inactive Ingredients

Camellia Sinensis leaf extract, centella asiatica extract, Chamomilla recutita (Matricaria) flower extract, Dimethyl sulfone, isopropyl myristate, Glycyrrhiza glabra (licorice) rooth extract, polygonum cuspidatum root extract, Rosmarinus officinais (rosemary) leaf extract, SD alcohol, Scutellaria caicalensis root extract, water.

Questions or Comments

Call 1-888-296-9067

Distributed By:

Trifecta Pharmaceuticals USA, LLC.

101 NE Third Avenue, Suite 1500

Ft. Lauderdale, FL. 33301 USA

www.trifecta-pharma.com

SKU: 6000

* This product is not manufactured or distributed by RB Health (US), the distributor of BioFreeze.